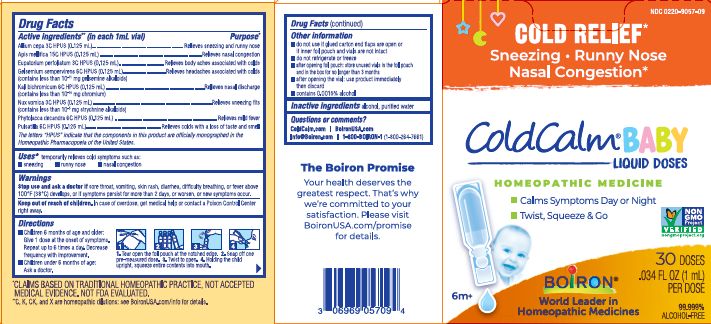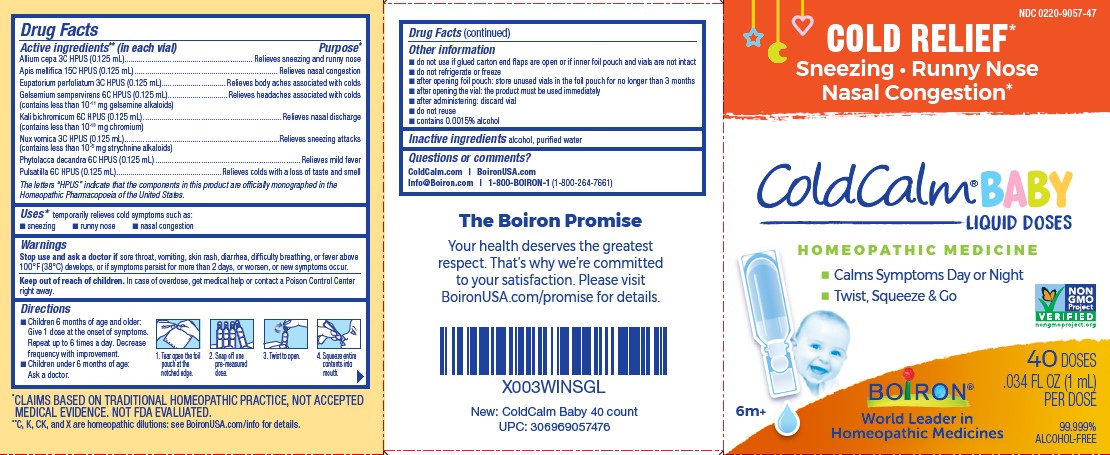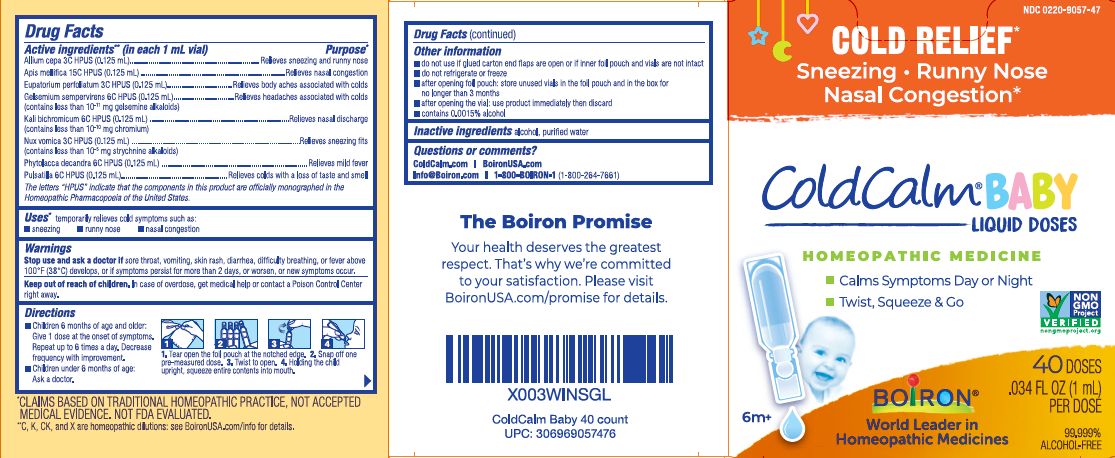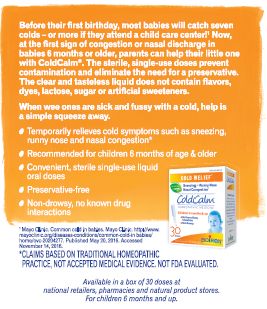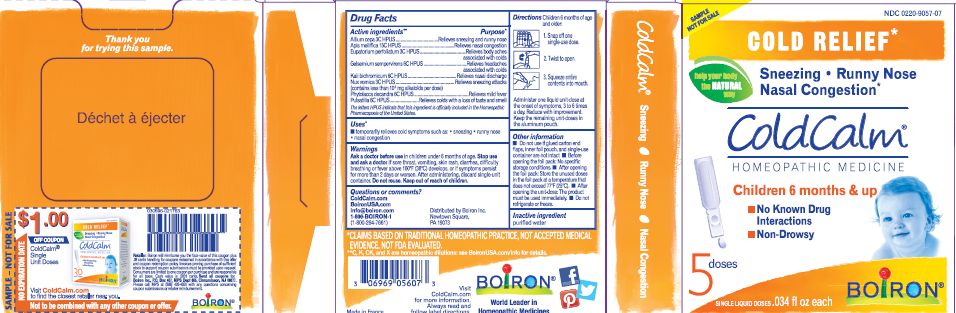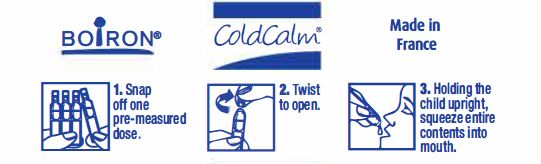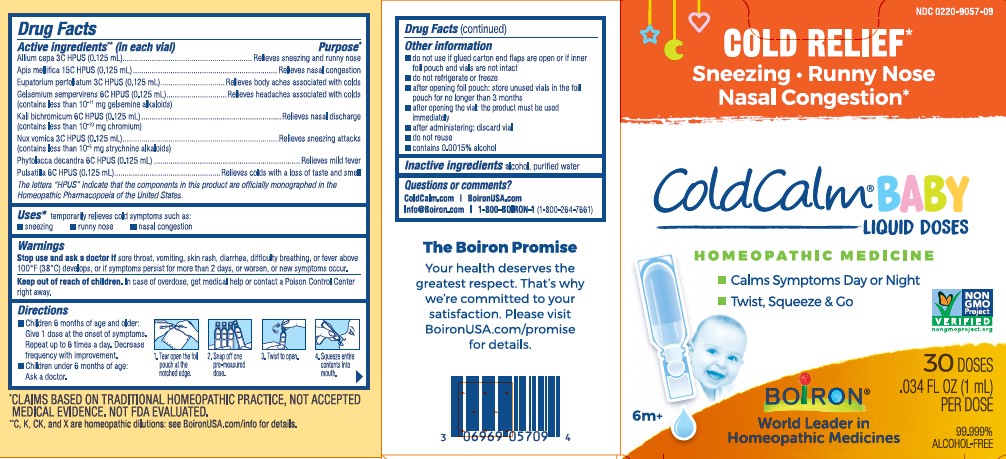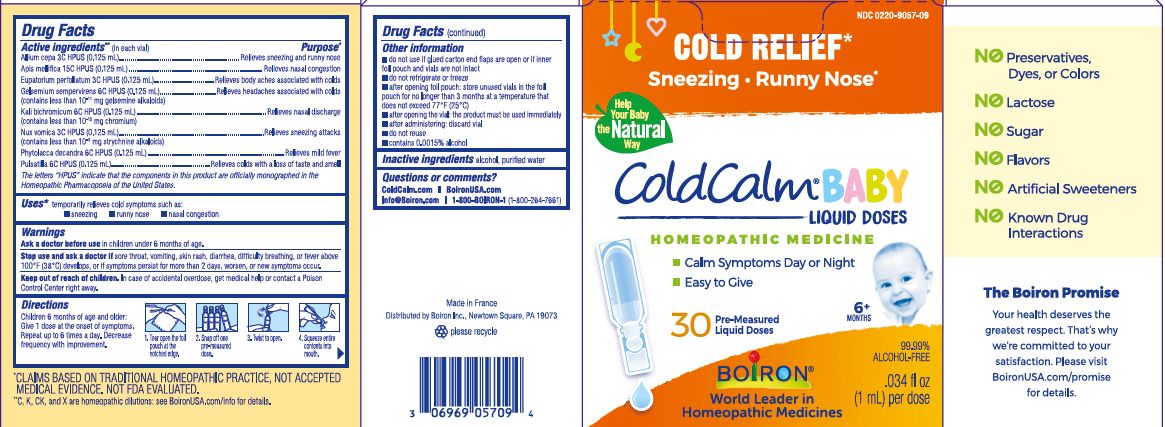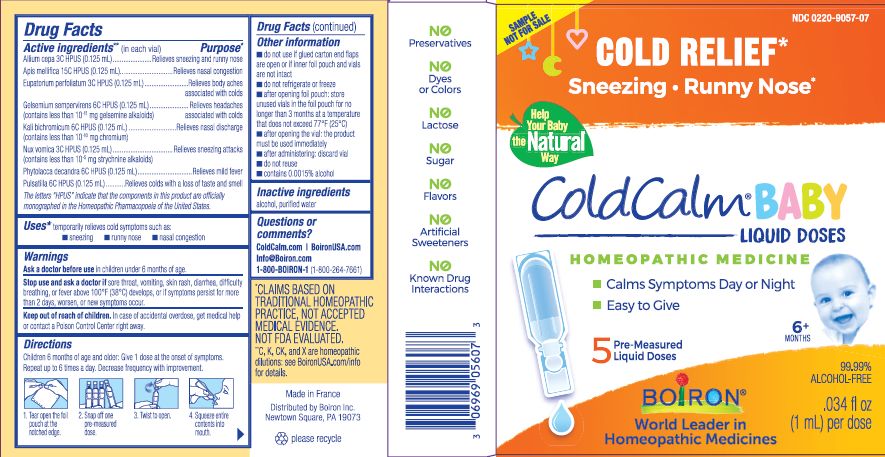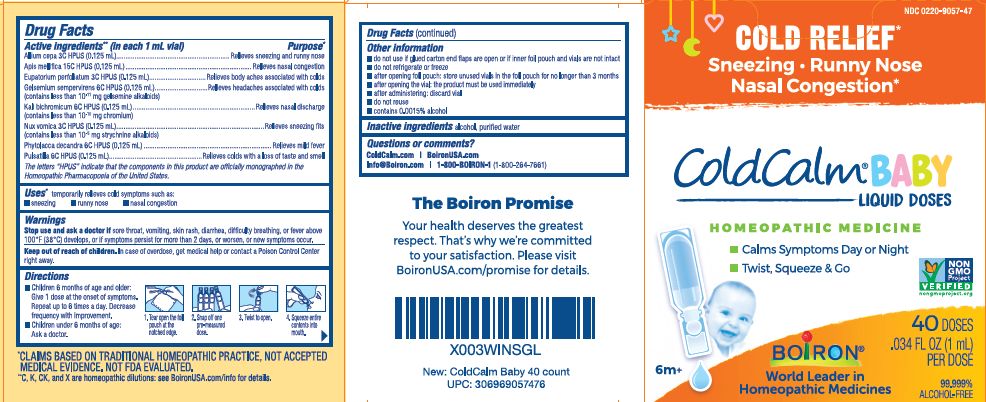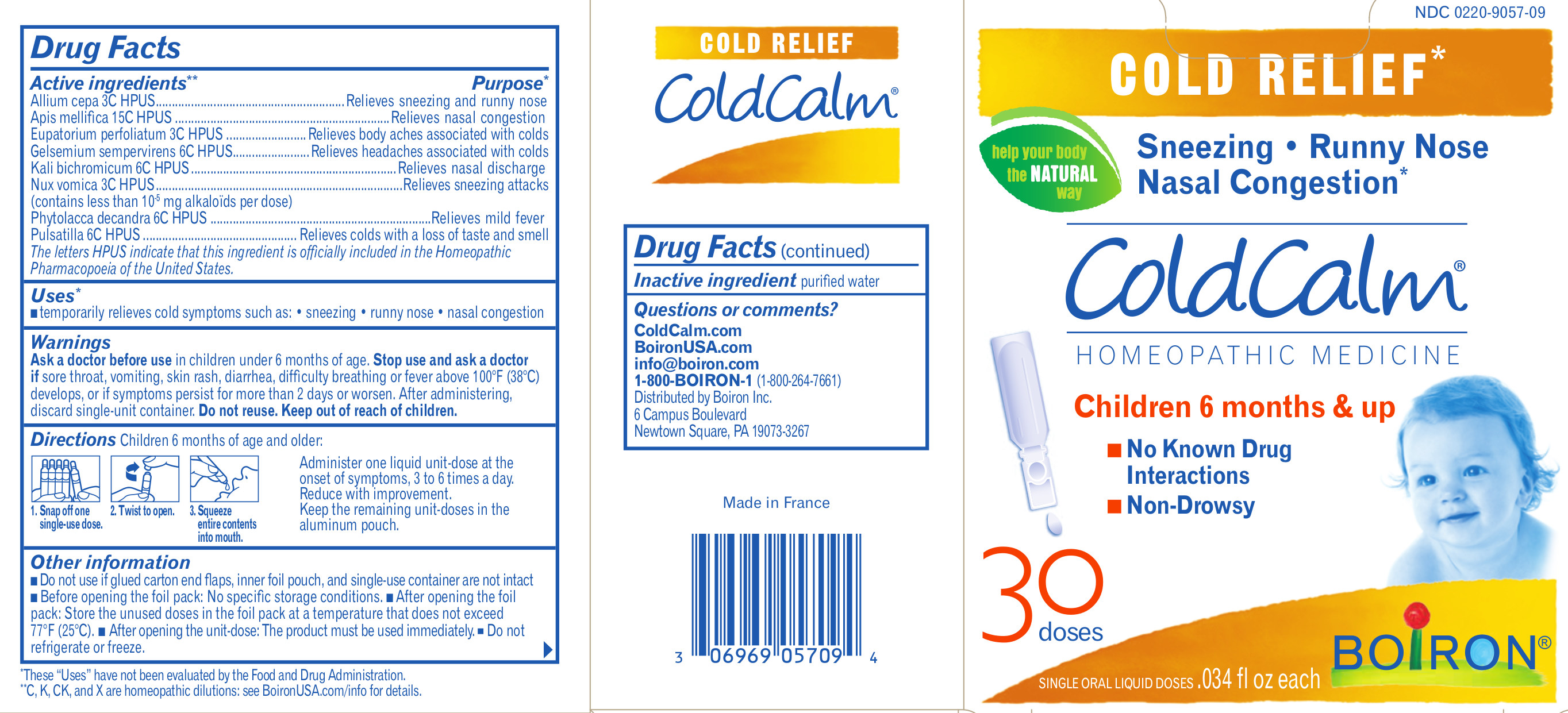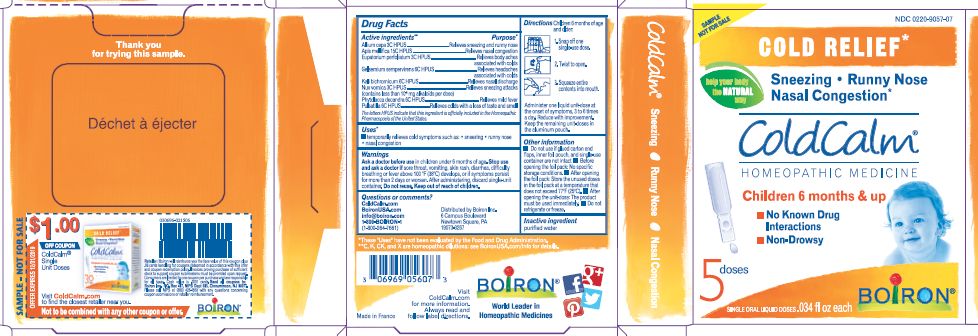 DRUG LABEL: Coldcalm
NDC: 0220-9057 | Form: LIQUID
Manufacturer: Laboratoires Boiron
Category: homeopathic | Type: HUMAN OTC DRUG LABEL
Date: 20250724

ACTIVE INGREDIENTS: ONION 3 [hp_C]/1 1; APIS MELLIFERA 15 [hp_C]/1 1; EUPATORIUM PERFOLIATUM FLOWERING TOP 3 [hp_C]/1 1; GELSEMIUM SEMPERVIRENS ROOT 6 [hp_C]/1 1; POTASSIUM DICHROMATE 6 [hp_C]/1 1; STRYCHNOS NUX-VOMICA SEED 3 [hp_C]/1 1; PHYTOLACCA AMERICANA ROOT 6 [hp_C]/1 1; PULSATILLA VULGARIS 6 [hp_C]/1 1
INACTIVE INGREDIENTS: WATER; ALCOHOL

Coldcalm Liquid

Active Ingredients

Active ingredients** (in each 1mL vial)

Allium cepa 3C HPUS (0.125 mL)

Apis mellifica 15C HPUS (0.125 mL)

Eupatorium perfoliatum 3C HPUS (0.125 mL)

Gelsemium sempervirens 6C HPUS (0.125 mL) (contains less than 10^-11 mg gelsemine alkaloids)

Kali bichromicum 6C HPUS (0.125 mL) (contains less than 10^-10 mg chromium)

Nux vomica 3C HPUS (0.125 mL) (contains less than 10^-5 mg strychnine alkaloids)

Phytolacca decandra 6C HPUS (0.125 mL)

Pulsatilla 6C HPUS (0.125 mL)

The letters "HPUS" indicate that the components in this product are officially monographed in the Homeopathic Pharmacopoeia of the United States.

Purpose

Allium cepa 3C HPUS ... Relieves sneezing and runny nose
Apis mellifica 15C HPUS ... Relieves nasal congestion
Eupatorium perfoliatum 3C HPUS ... Relieves body aches associated with colds
Gelsemium sempervirens 6C HPUS ... Relieves headaches associated with colds
Kali bichromicum 6C HPUS ... Relieves nasal discharge
Nux vomica 3C HPUS ... Relieves sneezing fits
Phytolacca decandra 6C HPUS ... Relieves mild fever
Pulsatilla 6C HPUS ... Relieves colds with a loss of taste and smell

Uses*

temporarily relieves cold symptoms such as:

- sneezing
- runny nose
- nasal congestion

WARNINGS

Stop use and ask doctor if sore throat, vomiting, skin rash, diarrhea, difficulty breathing, or fever above 100o F (38o C) develops, or if symptoms persist for more than 2 days or worsen, or new symptoms occur.

Keep out of reach of children. In case of overdose, get medical help or contact a Poison Control Center right away.

Directions

Children 6 months of age and older:

Give 1 dose at the onset of symptoms. Repeat up to 6 times a day. Decrease frequency with improvement.

Children under 6 months of age:

Ask a doctor.

1. Tear open the foil pouch at the notched edge.
2. Snap off one pre-measured dose.
3. Twist to open.
4. Holding the child upright, squeeze entire contents into mouth.

do not use if glued carton flaps are open or if inner foil pouch and vials are not intact

do not refrigerate or freeze

after opening foil pouch: store unused vials in the foil pouch for no longer than 3 months

after opening the vial: use product immediately then discard

contains 0.0015% alcohol

Cold Relief*

Sneezing, Runny Nose, Nasal Congestion*

No Known Drug Interactions

40 Pre-measured liquid doses 0.34 fl oz (1 mL) per dose

30 Pre-measured liquid doses 0.34 fl oz (1 mL) per dose

5 Pre-measured liquid doses 0.34 fl oz (1 mL) per dose

*CLAIMS BASED ON TRADITIONAL HOMEOPATHIC PRACTICE NOT ACCEPTED MEDICAL EVIDENCE. NOT FDA EVALUATED.
**C,K,CK, and X are homeopathic dilutions: see BoironUSA.com/info for details.

INACTIVE INGREDIENT

alcohol, purified water

Questions or comments?

ColdCalm.com
BoironUSA.com
info@boiron.com
1-800-BOIRON-1 (1-800-264-7661)
Distributed by Boiron Inc.
Newtown Square, PA 19073